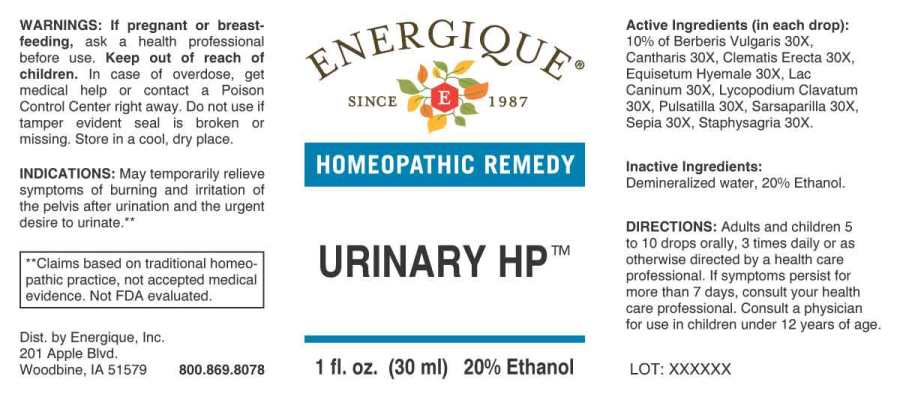 DRUG LABEL: Urinary HP
NDC: 44911-0596 | Form: LIQUID
Manufacturer: Energique, Inc.
Category: homeopathic | Type: HUMAN OTC DRUG LABEL
Date: 20241031

ACTIVE INGREDIENTS: SMILAX ORNATA ROOT 30 [hp_X]/1 mL; ARCTOSTAPHYLOS UVA-URSI LEAF 30 [hp_X]/1 mL; ARSENIC TRIOXIDE 30 [hp_X]/1 mL; LYTTA VESICATORIA 30 [hp_X]/1 mL; CHONDRODENDRON TOMENTOSUM ROOT 30 [hp_X]/1 mL; ANEMONE PULSATILLA 30 [hp_X]/1 mL; SEPIA OFFICINALIS JUICE 30 [hp_X]/1 mL; TURPENTINE OIL 30 [hp_X]/1 mL; POPULUS TREMULOIDES BARK 30 [hp_X]/1 mL; POPULUS TREMULOIDES LEAF 30 [hp_X]/1 mL
INACTIVE INGREDIENTS: WATER; ALCOHOL

Drug Facts:

ACTIVE INGREDIENTS:

(in each drop): 14.26% of Arsenicum Album 12X, Cantharis 12X, Pareira Brava 12X, Populus Tremuloides 15X Pulsatilla 12X, Sepia 12X, Terebinthina 12X; 0.10% of Sarsaparilla 3X, Uva Ursi 3X.

INDICATIONS:

May temporarily relieve intolerable urging, pressure in the area of the bladder, and having to urinate often.**

**Claims based on traditional homeopathic practice, not accepted medical evidence. Not FDA evaluated.

WARNINGS:

If pregnant or breast-feeding, ask a health professional before use.

Keep out of reach of children. In case of overdose, get medical help or contact a Poison Control Center right away.

Do not use if tamper evident seal is broken or missing.

Store in a cool, dry place.

Keep out of reach of children. In case of overdose, get medical help or contact a Poison Control Center right away.

DIRECTIONS:

Adults and children 5 to 10 drops orally, 3 times daily or as otherwise directed by a health care professional. If symptoms persist, consult your health care professional. Consult a physician for use in children under 12 years of age.

INDICATIONS:

May temporarily relieve intolerable urging, pressure in the area of the bladder, and having to urinate often.**

**Claims based on traditional homeopathic practice, not accepted medical evidence. Not FDA evaluated.

INACTIVE INGREDIENTS:

Demineralized Water, 20% Ethanol

QUESTIONS:

Dist. by Energique, Inc.

201 Apple Blvd.

Woodbine, IA 51579 800.869.8078

PACKAGE LABEL DISPLAY:

ENERGIQUE

SINCE 1987

HOMEOPATHIC REMEDY

URINARY HP

1 fl. oz. (30 ml)